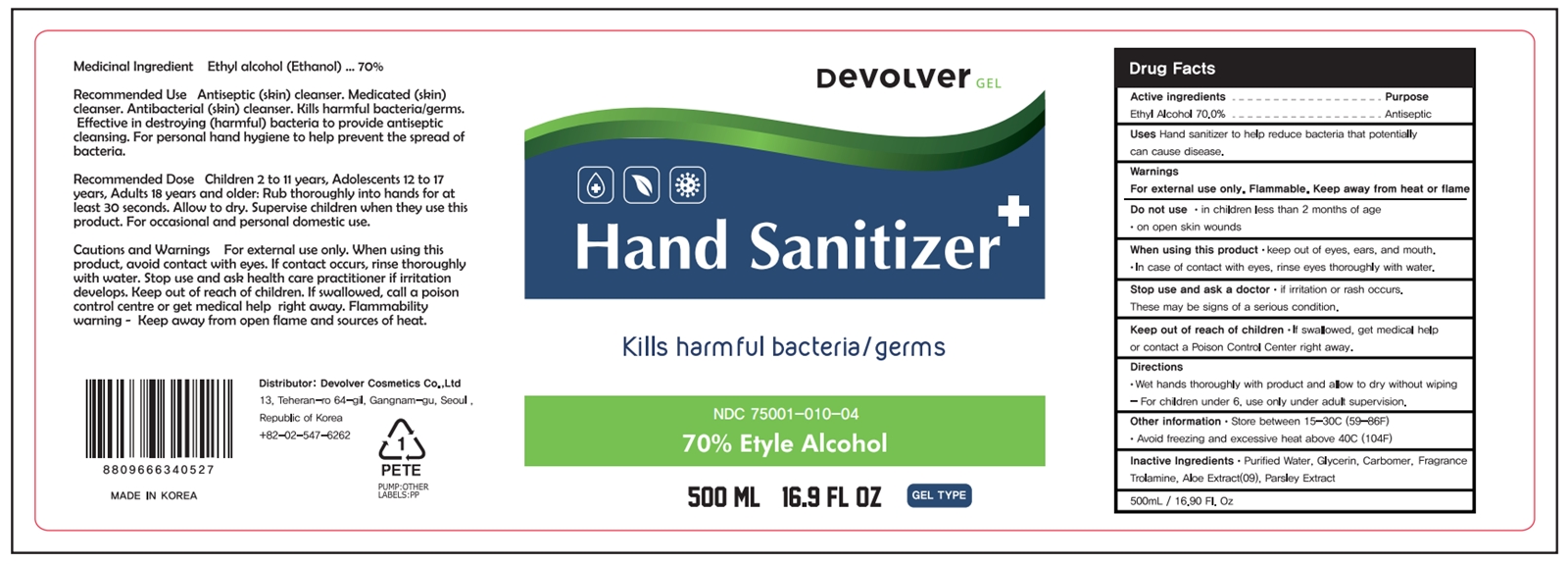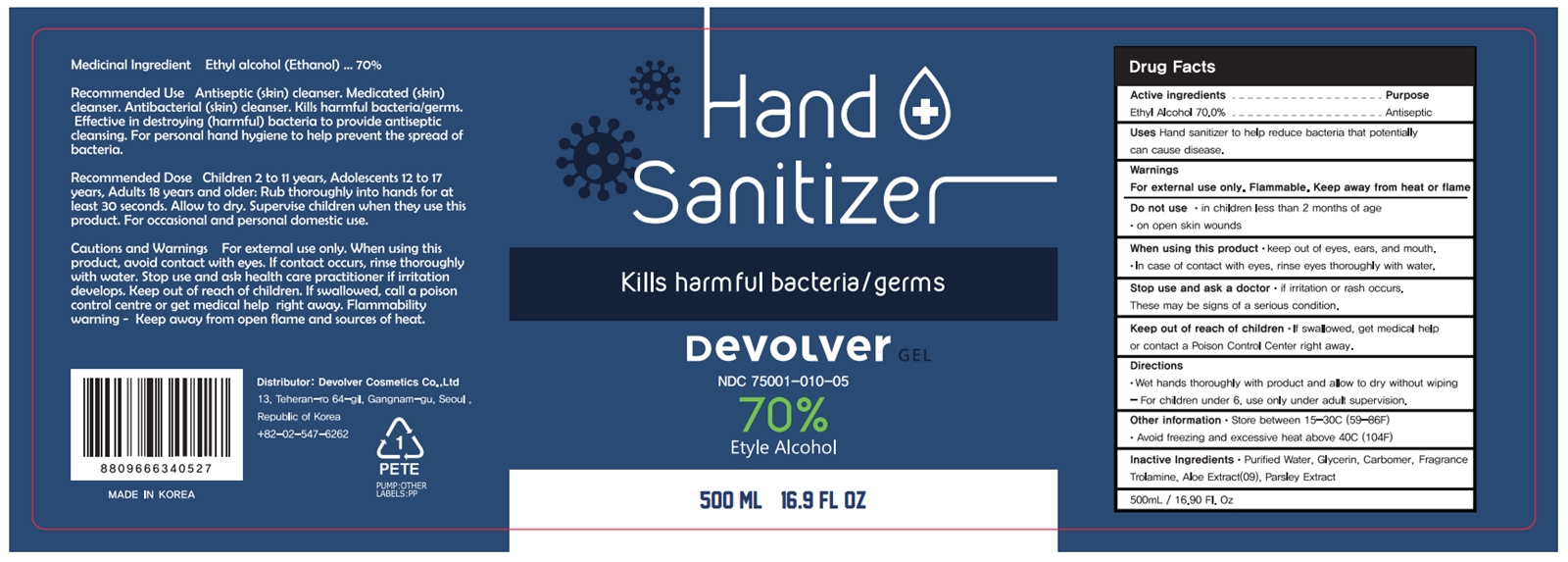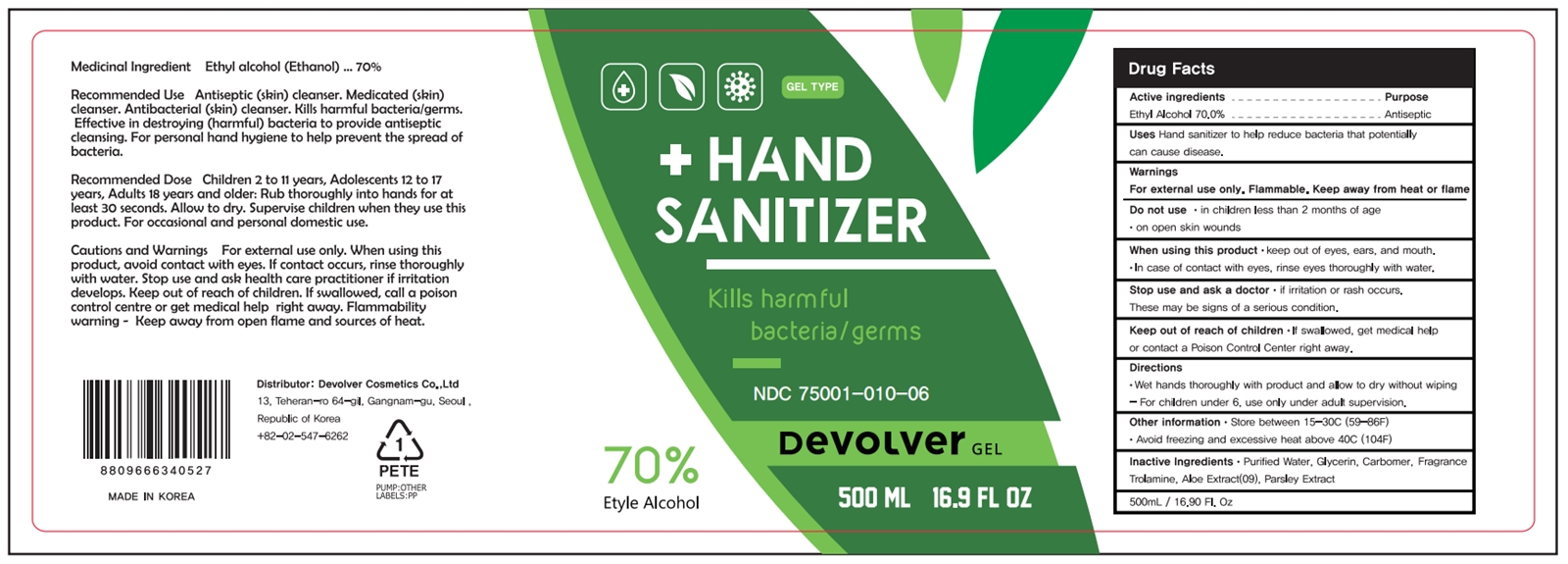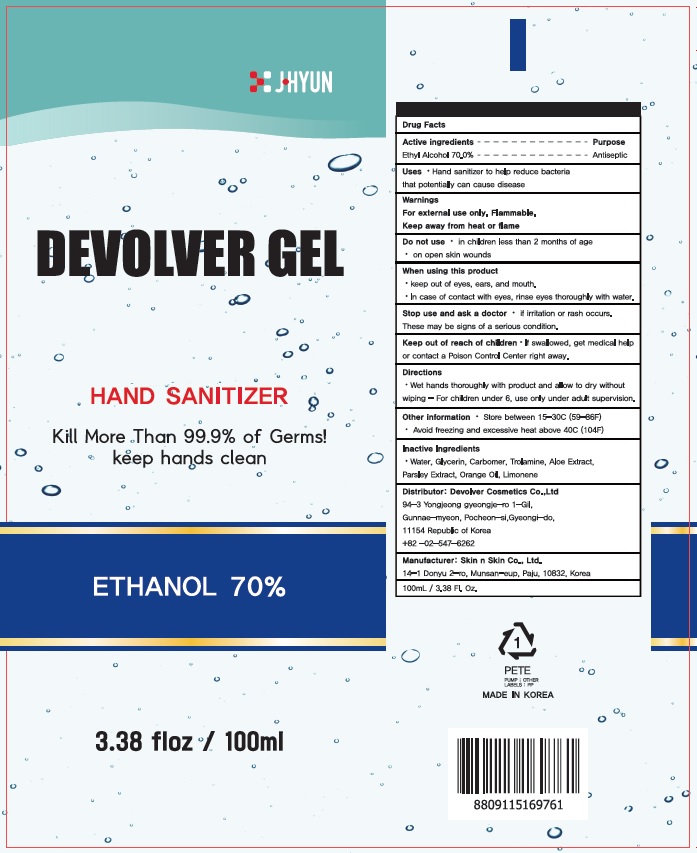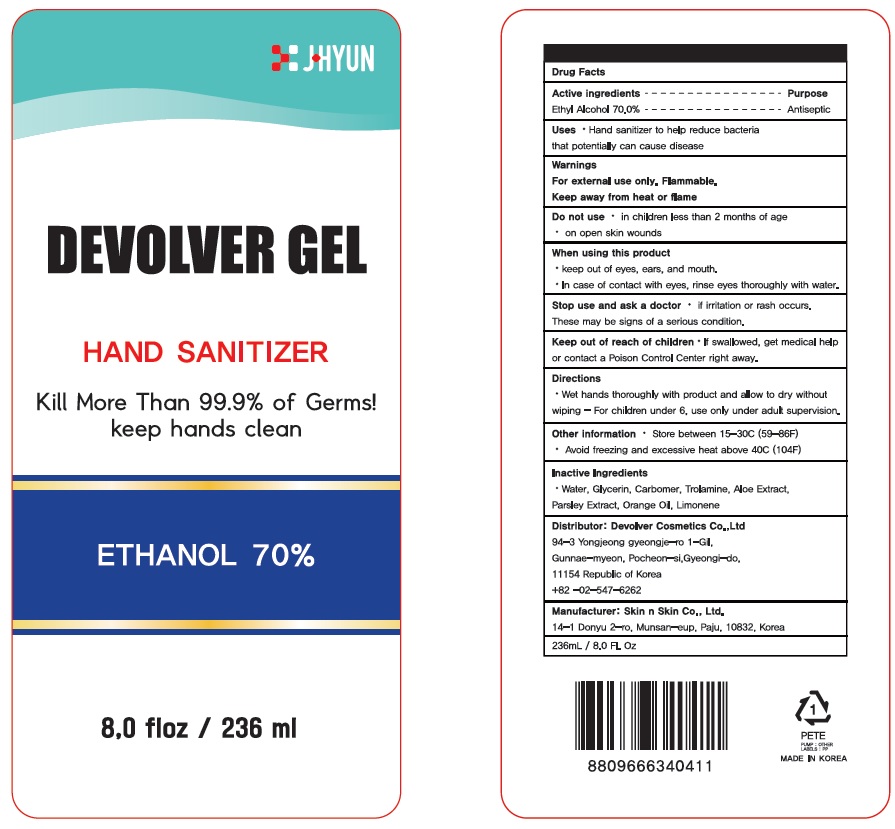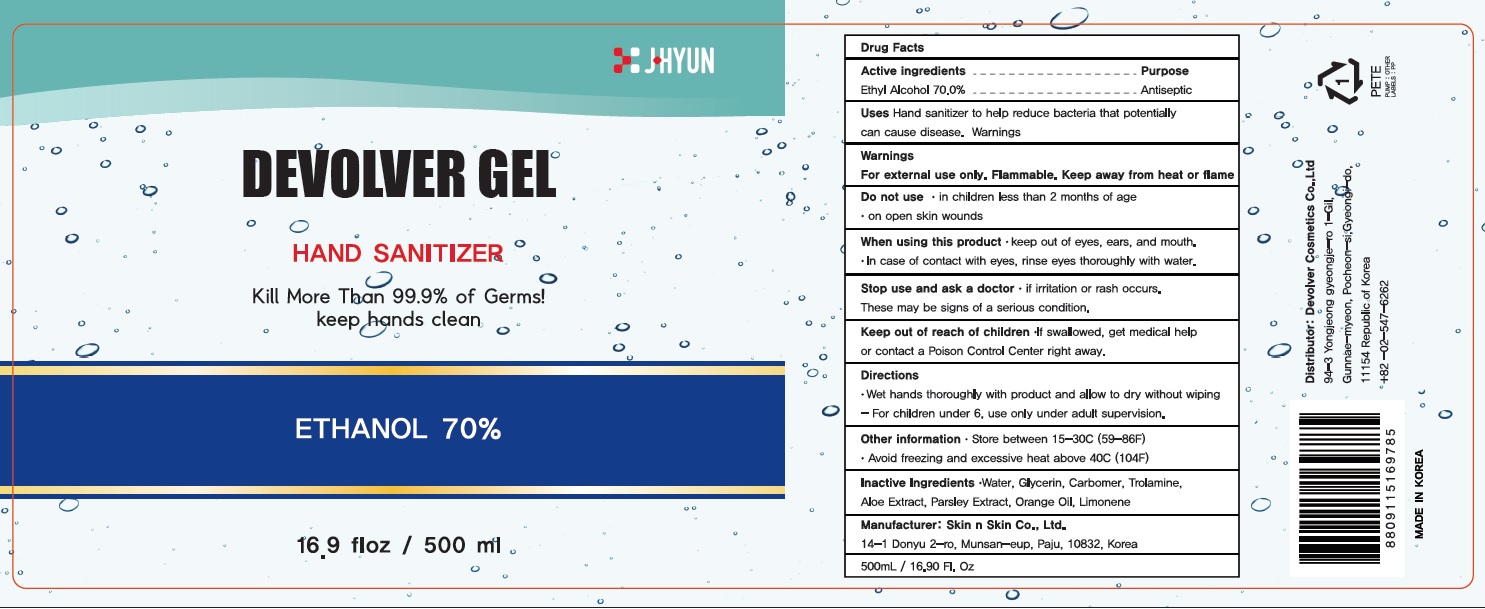 DRUG LABEL: Devolver Hand Sanitizer
NDC: 75001-010 | Form: GEL
Manufacturer: Devolver Cosmetics Co.,Ltd
Category: otc | Type: HUMAN OTC DRUG LABEL
Date: 20200609

ACTIVE INGREDIENTS: ALCOHOL 70 g/100 mL
INACTIVE INGREDIENTS: WATER; GLYCERIN; CARBOMER HOMOPOLYMER, UNSPECIFIED TYPE; TROLAMINE; ALOE; PARSLEY; ORANGE OIL; LIMONENE, (+)-

75001-010

ACTIVE INGREDIENT

Active ingredients
ETHANOL 70%

INACTIVE INGREDIENT

Inactive ingredients
Water, Glycerin, Carbomer, Trolamine, Aloe Extract, Parsley Extract, Orange Oil, Limonene

PURPOSE

Purpose: ANTISEPTIC

WARNINGS

For external use only. Flammable. Keep away from heat or flame
--------------------------------------------------------------------------------------------------------
Do not use
• in children less than 2 months of age
• on open skin wounds
--------------------------------------------------------------------------------------------------------
When using this product keep out of eyes, ears, and mouth. In case of contact with eyes, rinse eyes thoroughly with water.
--------------------------------------------------------------------------------------------------------
Stop use and ask a doctor if irritation or rash occurs. These may be signs of a serious condition.

Keep out of reach of children. If swallowed, get medical help or contact a Poison Control Center right away.

Uses

Hand sanitizer to help reduce bacteria that potentially can cause disease.

Directions

• Wet hands thoroughly with product and allow to dry without wiping - For children under 6, use only under adult supervision.

Other information

• Store between 15-30C (59-86F)
• Avoid freezing and excessive heat above 40C (104F)